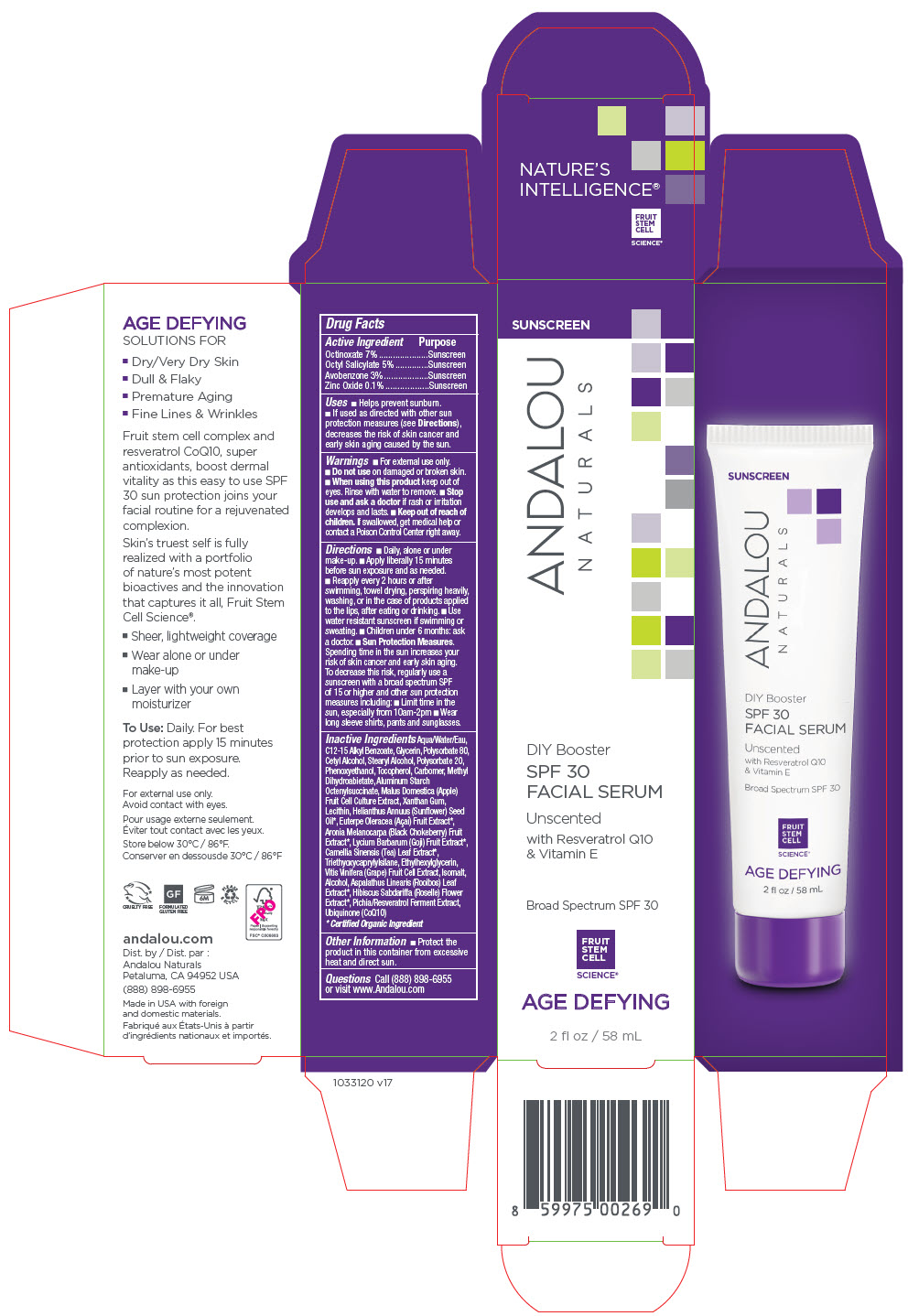 DRUG LABEL: DIY Booster SPF 30 Facial Serum Unscented
NDC: 55560-0107 | Form: LOTION
Manufacturer: Andalou naturals
Category: otc | Type: HUMAN OTC DRUG LABEL
Date: 20250609

ACTIVE INGREDIENTS: OCTINOXATE 70 mg/1 mL; OCTISALATE 50 mg/1 mL; AVOBENZONE 30 mg/1 mL; ZINC OXIDE 1 mg/1 mL
INACTIVE INGREDIENTS: WATER; ALKYL (C12-15) BENZOATE; GLYCERIN; POLYSORBATE 80; CETYL ALCOHOL; STEARYL ALCOHOL; POLYSORBATE 20; PHENOXYETHANOL; TOCOPHEROL; CARBOMER HOMOPOLYMER, UNSPECIFIED TYPE; METHYL DIHYDROABIETATE; ALUMINUM STARCH OCTENYLSUCCINATE; APPLE; XANTHAN GUM; SOYBEAN LECITHIN; SUNFLOWER OIL; ACAI; ARONIA MELANOCARPA FRUIT JUICE; LYCIUM BARBARUM FRUIT; TEA LEAF; TRIETHOXYCAPRYLYLSILANE; ETHYLHEXYLGLYCERIN; VITIS VINIFERA HIGH TANNIN CULTIVAR FRUIT CELL LYSATE; ISOMALT; ALCOHOL; ASPALATHUS LINEARIS LEAF; HIBISCUS SABDARIFFA FLOWER; RESVERATROL; UBIDECARENONE

DIY Booster SPF 30 Facial Serum Unscented

Drug Facts

ACTIVE INGREDIENT

Active Ingredient | Purpose
Octinoxate 7% | Sunscreen
Octisalate 5% | Sunscreen
Avobenzone 3% | Sunscreen
Zinc Oxide 0.1% | Sunscreen

Uses

- Helps prevent sunburn.

Warnings

- For external use only.

- Do not use on damaged or broken skin.

- When using this product keep out of eyes. Rinse with water to remove.

- Stop use and ask a doctor if rash or irritation develops and lasts.

- Keep out of reach of children. If swallowed, get medical help or contact a Poison Control Center right away.

Directions

- Daily, alone or under make-up.
- Apply liberally 15 minutes before sun exposure and as needed.
- Reapply every 2 hours or after swimming, towel drying, perspiring heavily, washing, or in the case of products applied to the lips, after eating or drinking.
- Use water resistant sunscreen if swimming or sweating.
- Sun Protection Measures. Spending time in the sun increases your risk of skin cancer and early skin aging. To decrease this risk, regularly use a sunscreen with a broad spectrum SPF of 15 or higher and other sun protection measures including: limit time in the sun, especially from 10am-2pm, wear long sleeve shirts, pants and sunglasses.
- Children under 6 months: ask a doctor.

Inactive Ingredients

Aqua/Water/Eau, C12-15 Alkyl Benzoate, Glycerin, Polysorbate 80, Cetyl Alcohol, Stearyl Alcohol, Polysorbate 20, Phenoxyethanol, Tocopherol, Carbomer, Methyl Dihydroabietate, Aluminum Starch Octenylsuccinate, Malus Domestica (Apple) Fruit Cell Culture Extract, Xanthan Gum, Lecithin, Helianthus Annuus (Sunflower) Seed Oil [Certified Organic Ingredient] , Euterpe Oleracea (Açaí) Fruit Extract, Aronia Melanocarpa (Black Chokeberry) Fruit Extract, Lycium Barbarum (Goji) Fruit Extract, Camellia Sinensis (Tea) Leaf Extract, Triethyoxycaprylylsilane, Ethylhexylglycerin, Vitis Vinifera (Grape) Fruit Cell Extract, Isomalt, Alcohol, Aspalathus Linearis (Rooibos) Leaf Extract, Hibiscus Sabdariffa (Roselle) Flower Extract, Pichia/Resveratrol Ferment Extract, Ubiquinone (CoQ10)

Other Information

- Protect the product in this container from excessive heat and direct sun.

Questions

Call (888) 898-6955 or visit www.Andalou.com

Dist. by Andalou Naturals
Novato, CA 94945 USA

PRINCIPAL DISPLAY PANEL - 58 mL Tube Carton

SUNSCREEN

ANDALOU
NATURALS

DIY Booster

SPF 30
FACIAL SERUM

Unscented

with Resveratrol Q10
& Vitamin E

Broad Spectrum SPF 30

FRUIT
STEM
CELL
SCIENCE®

AGE DEFYING

2 fl oz / 58 mL